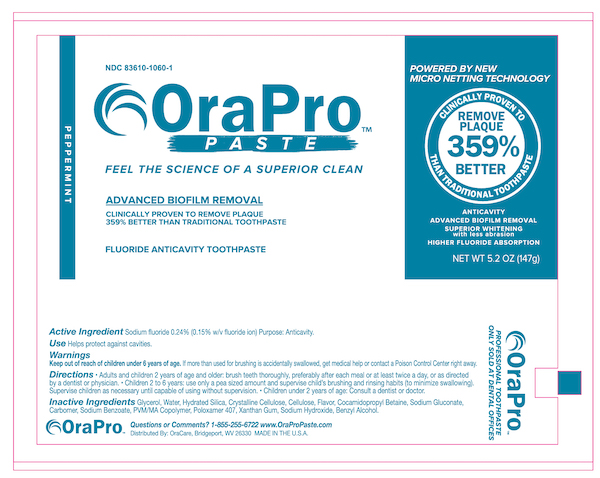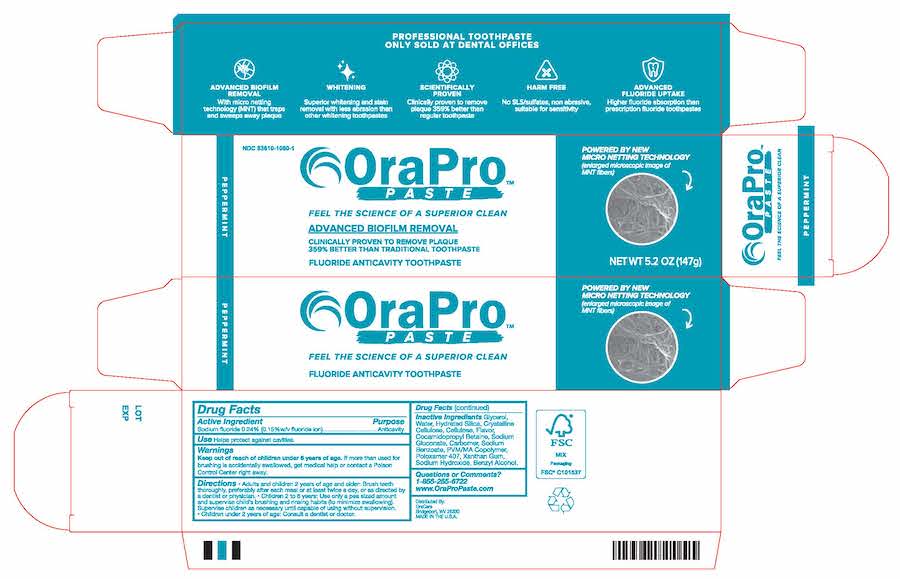 DRUG LABEL: OraPro Fluoride Anticavity
NDC: 83610-1060 | Form: PASTE, DENTIFRICE
Manufacturer: Protegera, Inc.
Category: otc | Type: HUMAN OTC DRUG LABEL
Date: 20250710

ACTIVE INGREDIENTS: SODIUM FLUORIDE 1.4 mg/1 g
INACTIVE INGREDIENTS: GLYCERIN; WATER; CELLULOSE GUM; CALCIUM CARBOXYMETHYL CELLULOSE; HYDRATED SILICA; COCAMIDOPROPYL BETAINE; SODIUM GLUCONATE; CARBOMER 980; SODIUM BENZOATE; METHYL VINYL ETHER AND MALEIC ACID COPOLYMER (1750000 WAMW); POLOXAMER 407; XANTHAN GUM; SODIUM HYDROXIDE; BENZYL ALCOHOL

OraPro Fluoride Anticavity Toothpaste

Active ingredient

Sodium Fluoride 0.24% (0.15% w/v fluoride ion)

Purpose

Anticavity

Use

Helps protect agaisnt cavities

Warnings

If more than used for brushing is accidently swallowed, get medical help or contact a Poison Control Center right away

Directions

adults and children 2 years of age and older: Brush teeth thoroughly, preferably after each meal or at least twice a day, or as directed by a dentist or physician. Children 2 to 6 years: Use only a pea sized amount and supervise child's brushing and rinsing habits (to minimize swallowing). Supervise children as nessary until capable of using without supervision. Children under 2 years ask a dentist or physician

Inactive ingredients:

Glycerol, Water, Hydrated Silica, Crystalline Cellulose, Cellulose, Flavor, Cocamidopropyl Betaine, Sodium Gluconate, Carbomer, Sodium Benzoate, PVM/MA Copolymer, Poloxamer 407, Xanthan Gum, Sodium Hydroxide, Benzyl Alcohol.

Principal Display Panel

OraPro Paste NDC 83610-1060-1

Advanced Biofilm Removal

Fluoride AnitCavity Toothpaste

NET WT 5.2 OZ (147g)